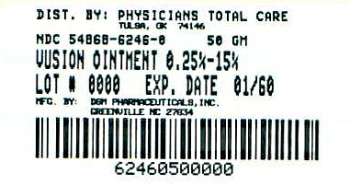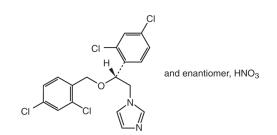 DRUG LABEL: VUSION
NDC: 54868-6246 | Form: OINTMENT
Manufacturer: Physicians Total Care, Inc.
Category: prescription | Type: HUMAN PRESCRIPTION DRUG LABEL
Date: 20110420

ACTIVE INGREDIENTS: MICONAZOLE NITRATE 2.5 mg/1 g; ZINC OXIDE 150 mg/1 g; PETROLATUM 813.5 mg/1 g
INACTIVE INGREDIENTS: BUTYLATED HYDROXYTOLUENE; GLYCOL STEARATE

HIGHLIGHTS OF PRESCRIBING INFORMATION

These highlights do not include all the information needed to use VUSION Ointment safely and effectively. See full prescribing information for VUSION Ointment. VUSION® (miconazole nitrate, zinc oxide, and white petrolatum) Ointment, for topical use only Initial U.S. Approval: 2006

1 INDICATIONS AND USAGE

- VUSION Ointment is indicated for adjunctive treatment of diaper dermatitis when complicated by documented candidiasis (microscopic evidence of pseudohyphae and /or budding yeast) in immunocompetent pediatric patients 4 weeks and older. (1)
- VUSION Ointment should not be used as a substitute for frequent diaper changes. (1)
- VUSION Ointment should not be used to prevent the occurrence of diaper dermatitis, since preventative use may result in the development of drug resistance. (1)

2 DOSAGE AND ADMINISTRATION

- VUSION Ointment is for topical use only. VUSION Ointment is not for oral, ophthalmic, or intravaginal use. (2)
- VUSION Ointment should be applied as a thin layer to the affected area at each diaper change for 7 days. (2)
- VUSION Ointment should be used as part of a treatment regimen that includes gentle cleansing of the diaper area and frequent diaper changes. (2)

3 DOSAGE FORMS AND STRENGTHS

- Ointment with 0.25% miconazole nitrate, 15% zinc oxide, and 81.35% white petrolatum. (3)

4 CONTRAINDICATIONS

- None

5 WARNINGS AND PRECAUTIONS

- If irritation occurs or if the disease worsens, discontinue use of the medication, and contact the health care provider. (5)

6 ADVERSE REACTIONS

To report SUSPECTED ADVERSE REACTIONS, contact Stiefel Laboratories, Inc. at 1-866-440-5508 or FDA at 1-800-FDA-1088 or www.fda.gov/medwatch.

FULL PRESCRIBING INFORMATION

1 INDICATIONS AND USAGE

Enter section text here

1.1 Indication

VUSION Ointment is indicated for the adjunctive treatment of diaper dermatitis only when complicated by documented candidiasis (microscopic evidence of pseudohyphae and/or budding yeast), in immunocompetent pediatric patients 4 weeks and older. A positive fungal culture for Candida albicans is not adequate evidence of candidal infection since colonization with C. albicans can result in a positive culture. The presence of candidal infection should be established by microscopic evaluation prior to initiating treatment.

VUSION should be used as part of a treatment regimen that includes measures directed at the underlying diaper dermatitis, including gentle cleansing of the diaper area and frequent diaper changes.

VUSION should not be used as a substitute for frequent diaper changes. VUSION should not be used to prevent the occurrence of diaper dermatitis, since preventative use may result in the development of drug resistance.

1.2 Limitations of Use

The safety and efficacy of VUSION have not been demonstrated in immunocompromised patients, or in infants less than 4 weeks of age (premature or term).

The safety and efficacy of VUSION have not been evaluated in incontinent adult patients. VUSION should not be used to prevent the occurrence of diaper dermatitis, such as in an adult institutional setting, since preventative use may result in the development of drug resistance.

2 DOSAGE AND ADMINISTRATION

VUSION is not for oral, ophthalmic, or intravaginal use.

Before applying VUSION, gently cleanse the skin with lukewarm water and pat dry with a soft towel. Avoid using any scented soaps, shampoos, or lotions on the diaper area.

Apply VUSION to the affected area at each diaper change for 7 days. Continue treatment for the full 7 days, even if there is improvement. The safety of VUSION when used for longer than 7 days is not known. Do not use VUSION for longer than 7 days. If symptoms have not improved by day 7, see your health care provider.

Gently apply a thin layer of VUSION to the diaper area with the fingertips. Do not rub VUSION into the skin as this may cause additional irritation. Thoroughly wash hands after applying VUSION.

3 DOSAGE FORMS AND STRENGTHS

White ointment containing 0.25% miconazole nitrate, 15% zinc oxide, and 81.35% white petrolatum.

4 CONTRAINDICATIONS

None

5 WARNINGS AND PRECAUTIONS

If irritation occurs or if the disease worsens, discontinue use of the medication, and contact the health care provider.

The safety and efficacy of VUSION have not been evaluated in incontinent adult patients. VUSION should not be used to prevent the occurrence of diaper dermatitis, such as in an adult institutional setting, since preventative use may result in the development of drug resistance.

6 ADVERSE REACTIONS

Enter section text here

6.1 Clinical Trials Experience

Because clinical trials are conducted under widely varying conditions, adverse reaction rate observed in the clinical trials of a drug cannot be directly compared to rates in the clinical trials of another drug and may not reflect the rates observed in clinical practice.

A total of 835 infants and young children were evaluated in the clinical development program. Of 418 subjects in the VUSION group, 58 (14%) reported one or more adverse events. Of 417 subjects in the zinc oxide/white petrolatum control group, 85 (20%) reported one or more adverse events. Adverse events that occurred at a rate of ≥ 1% for subjects who were treated with VUSION were approximately the same in type and frequency as for subjects who were treated with zinc oxide/white petrolatum ointment.

6.2 Post-marketing Experience

The following adverse reactions have been identified during post approval use of VUSION.

GASTROINTESTINAL DISORDERS: vomiting

GENERAL DISORDERS AND ADMINISTRATION SITE CONDITIONS: burning sensation, condition aggravated, inflammation, pain

INJURY, POISONING AND PROCEDURAL COMPLICATIONS: accidental exposure

SKIN AND SUBCUTANEOUS TISSUE DISORDERS: blister, dermatitis contact, diaper dermatitis, dry skin, erythema, pruritus, rash, skin exfoliation

Because these reactions are reported voluntarily from a population of uncertain size, it is not always possible to reliably estimate their frequency or establish a causal relationship to drug exposure.

7 DRUG INTERACTIONS

Drug-drug interaction studies were not conducted. Women who take a warfarin anticoagulant and use a miconazole intravaginal cream or suppository may be at risk for developing an increased prothrombin time, international normalized ratio (INR), and bleeding. The potential for this interaction between warfarin and VUSION is unknown.

8 USE IN SPECIFIC POPULATIONS

Enter section text here

8.1 Pregnancy

Pregnancy Category C

There are no adequate and well-controlled studies of VUSION in pregnant women. Therefore, VUSION should be used during pregnancy only if the potential benefit justifies the potential risk to the fetus.

Miconazole nitrate administration has been shown to result in prolonged gestation and decreased numbers of live young in rats and in increased number of resorptions and decreased number of live young in rabbits at oral doses of 100 mg/kg/day and 80 mg/kg/day, which are 28 and 45 times the maximum possible topical exposure of caregivers, respectively, assuming 100% absorption.

8.3 Nursing Mothers

Safety and efficacy of VUSION have not been established in nursing mothers. It is not known if the active components of VUSION may be present in milk.

8.4 Pediatric Use

Efficacy was not demonstrated in infants less than 4 weeks of age. Safety and efficacy have not been established in very-low-birth-weight infants.

VUSION should not be used to prevent diaper dermatitis.

The safety of VUSION when used for longer than 7 days is not known. Do not use more than 7 days.

8.5 Geriatric Use

Safety and efficacy in a geriatric population have not been evaluated.

11 DESCRIPTION

VUSION contains the synthetic antifungal agent, miconazole nitrate (0.25%) USP, zinc oxide (15%) USP, and white petrolatum (81.35%) USP.

The chemical name of miconazole nitrate is 1-[2, 4-dichloro-ß-{(2,4-dichlorobenzyl)oxy} phenethyl] imidazole mononitrate with empirical formula C18H14Cl4N2O•HNO3 and molecular weight of 479.15. The structural formula of miconazole nitrate is as follows:

The zinc oxide has an empirical formula of ZnO and a molecular weight of 81.39.

The white petrolatum, which is obtained from petroleum and is wholly or nearly decolorized, is a purified mixture of semisolid saturated hydrocarbons having the general chemical formula CnH2n+2. The hydrocarbons consist mainly of branched and unbranched chains. White petrolatum contains butylated hydroxytoluene (BHT) as stabilizer.

Each gram of VUSION contains 2.5 mg of miconazole nitrate USP, 150 mg of zinc oxide USP, and 813.5 mg of white petrolatum USP containing butylated hydroxytoluene, trihydroxystearin, and Chemoderm® 1001/B fragrance.^1

VUSION is a smooth, uniform, white ointment.

12 CLINICAL PHARMACOLOGY

Enter section text here

12.1 Mechanism of Action

The miconazole component of VUSION is an antifungal agent [see Clinical Pharmacology (12.4)]. The mechanism of action of white petrolatum and zinc oxide for the adjunctive treatment of diaper dermatitis is unknown.

12.2 Pharmacodynamics

The human pharmacodynamics of Vusion is unknown [see Clinical Pharmacology (12.4) for fungal pharmacodynamics].

12.3 Pharmacokinetics

The topical absorption of miconazole from VUSION was studied in immunocompetent male and female infants and children (n=17) with diaper dermatitis complicated by documented candidiasis (microscopic evidence of pseudohyphae and/or budding yeast) ranging in age from 1 month to 21 months. After multiple daily applications to the affected area at every diaper change (approximately 5-12 times per day) for 7 days, the plasma concentrations of miconazole were below the lower limit of quantitation (LOQ) of 0.5 ng/mL in 15 out of 17 (88%) subjects. In the other 2 remaining subjects, the plasma concentrations of miconazole were 0.57 and 0.58 ng/mL, respectively at a single timepoint (4 hours after the last application) on Day 7.

12.4 Microbiology

The miconazole nitrate component in this product has been shown to have in vitro activity against Candida albicans, an organism that is associated with diaper dermatitis. The activity of miconazole nitrate against C. albicans is based on the inhibition of the ergosterol biosynthesis in the cell membrane. The accumulation of ergosterol precursors and toxic peroxides results in cytolysis of the cell. In vitro minimal inhibitory concentration (MIC) test results for C. albicans isolates obtained from treatment failures in Clinical Study 1 (see Clinical Studies (14)) does not appear to indicate that resistance to miconazole nitrate was the reason for treatment failure. The clinical significance of the in vitro activity of miconazole nitrate against C. albicans in the setting of diaper dermatitis is unclear.

13 NONCLINICAL TOXICOLOGY

Enter section text here

13.1 Carcinogenesis, Mutagenesis, Impairment of Fertility

The carcinogenic potential of VUSION in animals has not been evaluated.

Miconazole nitrate was negative in a bacterial reverse mutation test, a chromosome aberration test in mice, and micronucleus assays in mice and rats.

Miconazole nitrate had no adverse effect on fertility in a study in rats at oral doses of up to 320 mg/kg/day, which is 89 times the maximum possible topical exposure of caregivers, assuming 100% absorption.

14 CLINICAL STUDIES

Study 1 was a double-blind, multicenter study in which VUSION was compared to the zinc oxide and white petrolatum combination treatment and included 236 infants and toddlers with diaper dermatitis, complicated by candidiasis as documented by KOH tests that demonstrated psuedohyphae and/or budding yeasts. Study medication was applied at every diaper change for 7 days.

The primary endpoint was “Overall Cure” and required that subjects be both clinically cured (total resolution of all signs and symptoms of infection) and microbiologically cured (eradication of candidiasis). Primary efficacy was assessed 1 week following the end of treatment, at Day 14.

Study results are shown in the following table.

Overall Cure at Day 14
 | VUSION; n=112 | Zinc Oxide/White Petrolatum; n=124
 | 26 (23%) | 12 (10%)

Two additional studies provided supportive evidence of the clinical efficacy of VUSION in infants and toddlers with diaper dermatitis, some of whom cultured positive for C. albicans. However, candidal infection was not documented in the culture-positive subjects, as microscopic testing (e.g. KOH) was not done. Therefore, the positive culture results may have reflected colonization rather than infection.

16 HOW SUPPLIED/STORAGE AND HANDLING

Enter section text here

16.1 How Supplied

VUSION is a smooth, uniform, white ointment supplied in an aluminum tube, as follows:

50g (NDC 54868-6246-0)

16.2 Storage Conditions

Store at controlled room temperature between 20°C and 25°C (68°F and 77°F); with excursions permitted between 15°C and 30°C (59°F and 86°F).

Keep out of reach of children.

17 PATIENT COUNSELING INFORMATION

See FDA-Approved Patient Labeling

Patients using VUSION should be informed about the following information:

- VUSION is to be used only for diaper dermatitis that is complicated by documented candidiasis (i.e. documented by microscopic testing).
- VUSION should not be used as a substitute for frequent diaper changes.
- VUSION should not be used to prevent diaper dermatitis.
- VUSION should not be used long term.
- VUSION should be used only as directed by the health care provider.
- VUSION is for external use only. It is not for oral, ophthalmic, or intravaginal use.
- Gently cleanse the diaper area with lukewarm water or a very mild soap and pat the area dry with a soft towel before applying VUSION.
- Gently apply VUSION to the diaper area with the fingertips after each diaper change. Do not rub VUSION into the skin as this may cause additional irritation.
- Thoroughly wash hands after applying VUSION.
- Treatment should be continued for 7 days, even if there is improvement. Do not use VUSION for longer than 7 days. If symptoms have not improved by day 7, see your health care provider.
- VUSION should not be used on children for whom it is not prescribed.

VSN:2PI

FDA-Approved Patient Labeling

VUSION® (Vu-sion) Ointment

(0.25% miconazole nitrate, 15% zinc oxide and 81.35% white petrolatum)

IMPORTANT: For Skin Use Only. Do not use in the mouth, eyes, or vagina.

Read the Patient Information that comes with VUSION before you use it on your child. This leaflet does not take the place of talking to your health care provider about your child’s medical condition or treatment. If you have any questions or if you are not sure about any of the information on VUSION, ask your health care provider, or pharmacist.

What is VUSION?

VUSION is a prescription skin medicine used to treat diaper rash that also has a yeast infection in children who are at least 4 weeks old and who have a normal immune system. VUSION contains medicines that will help treat the yeast infection and the diaper rash, but you must also change your child’s diapers very often so that your child is not wearing a wet or soiled diaper. Even if you use VUSION, diaper rash will not go away if you do not keep your child’s diaper area clean and dry. You should use water or a very mild cleanser to clean your child’s diaper area. VUSION is not to be used to prevent diaper rash or to be used for more than 7 days.

Your health care provider will need to do a special test to tell if your child’s diaper rash also has a yeast infection. Do not use VUSION on your child’s diaper rash unless your health care provider tells you that there is also a yeast infection.

Who should not use VUSION?

VUSION is not for treatment of all cases of diaper rash. VUSION is only for diaper rash that also has a yeast infection. Most cases of diaper rash do not need the yeast medicine that is in VUSION because most cases of diaper rash do not also have a yeast infection.

Do not use VUSION on any other children or other family member.

Do not use VUSION on your child’s diaper rash if they are allergic to anything in it. See the end of this leaflet for a list of ingredients in VUSION.

Do not use on infants less than 4 weeks of age.

Do not use in infants or children who do not have a normal immune system.

How should I use VUSION on my child?

VUSION is applied to the skin on your child’s diaper area at each diaper change for 7 days.

Apply VUSION for the full 7 days even if the diaper rash starts to go away. Call your child’s health care provider if the diaper rash gets worse or does not go away with 7 days of treatment with VUSION. VUSION should not be used for more than 7 days.

To apply VUSION:

- Gently, clean the skin on your child’s diaper area with warm (not hot) water. You may also use a very mild soap. Pat the area dry with a soft towel.
- Use your fingertips and gently apply a thin layer of VUSION to your child’s diaper area at each diaper change. Do not rub VUSION into your child’s skin. Rubbing the skin can cause more irritation.
- Wash your hands after applying VUSION on your child.

VUSION is for skin use only.

Call your child’s health care provider or poison control center right away if any VUSION is swallowed. Call your child’s health care provider if VUSION gets in the eye.

Keep out of reach of children.

What other steps will help diaper rash go away?

- Check your child’s diaper often. Change the diaper at the first sign of wetness.
- Clean your child’s diaper area after each diaper change. Gently wipe the diaper area from the front to back using warm (not hot) water. You may also use a mild soap. Rinse the diaper area well. Pat dry with a soft towel.
- Keep the diaper area open to air when possible.
- Even if you use VUSION, diaper rash will not go away if you do not keep your child’s diaper area clean and dry.

What are the possible side effects of VUSION?

VUSION may cause irritation. You should call your child’s health care provider if irritation appears or if the diaper rash gets worse.

How should I store VUSION?

- Keep VUSION out of the reach of children to avoid the risk of accidental ingestion.
- Store VUSION at room temperature between 68°F to 77°F (20°C to 25°C).

General information about VUSION

Medicines are sometimes prescribed for conditions that are not mentioned in patient information leaflets.

Do not use VUSION for a condition for which it was not prescribed. Do not give VUSION to other children or family members, even if they have the same symptoms your child has. It may harm them.

This leaflet summarizes the most important information about VUSION. If you would like more information, talk to your child’s health care provider. You can ask your child’s health care provider or pharmacist for information about VUSION that is written for healthcare professionals.

Side effects may be reported to Stiefel Laboratories, Inc. at 1-866-440-5508 or the FDA at 1-800-FDA-1088.

What are the ingredients in VUSION?

Active Ingredients: miconazole nitrate, zinc oxide, and white petrolatum

Inactive Ingredients: trihydroxystearin, butylated hydroxyltoluene (BHT), and Chemoderm® 1001/B fragrance

This Patient Information leaflet has been approved by the U.S. Food and Drug Administration.

The Patient Information leaflet was last revised: January 2010

VSN:2PIL

Manufactured for:

Stiefel Laboratories, Inc.

Coral Gables, FL 33134 USA

Manufactured by:

DSM Pharmaceuticals, Inc.

Greenville, NC 27834

VUSION, STIEFEL, and STIEFEL & Design are registered trademarks of Stiefel Laboratories, Inc.

^1Chemoderm is a registered trademark of Firmenich Inc.

©2010 Stiefel Laboratories, Inc.

Revised March 2010

SAP#

P/N #

Relabeling of "Additional" barcode label by;

Physicians Total Care, Inc.
Tulsa, OK 74146

PRINCIPAL DISPLAY PANEL

NDC 0145-0002-04

Vusion®

(miconazole nitrate 0.25% USP, zinc oxide 15% USP, white petrolatum 81.35% USP)

Ointment

50 grams

Rx only

For topical use only

Usual Dosage: See package insert.

Caution: Not for oral, ophthalmic, or intravaginal use. Keep out of reach of children. If seal is damaged or punctured, do not use, and return product to place of purchase.

Description: Each gram of VUSION® Ointment contains 2.5 mg miconazole nitrate USP, 150 mg zinc oxide USP, and 813.5 mg white petrolatum USP containing butylated hydroxytoluene, trihydroxystearin, and Chemoderm® 1001/B fragrance.

Store at 15oC (77oF); excursions permitted to 25oC -30oC (59oF -86oF).

See tube crimp for lot number and expiration date.